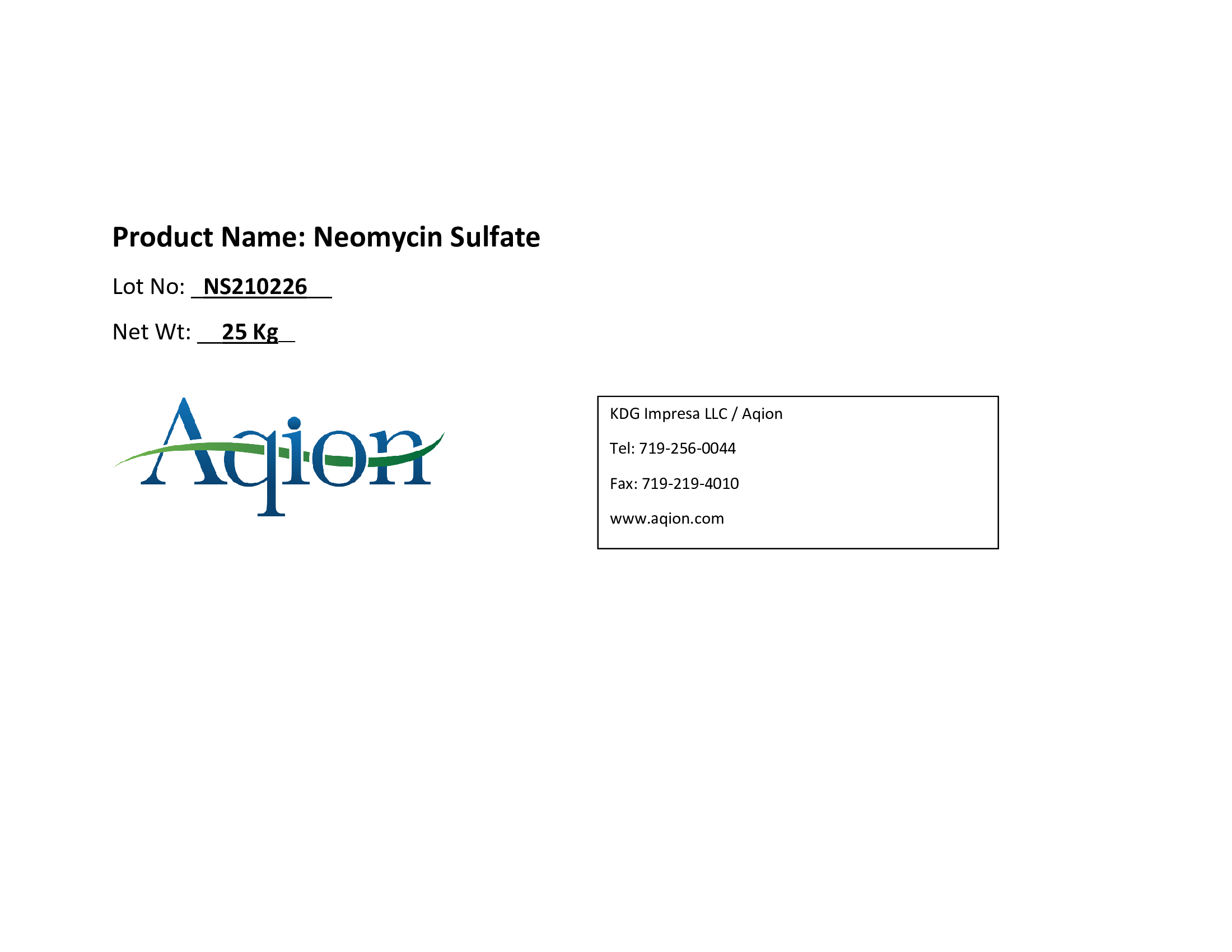 DRUG LABEL: Neomycin Sulfate
NDC: 43457-538 | Form: POWDER
Manufacturer: KDG Impresa LLC, Aqion
Category: other | Type: BULK INGREDIENT - ANIMAL DRUG
Date: 20220222

ACTIVE INGREDIENTS: NEOMYCIN SULFATE 1 kg/1 kg

Neomycin Sulfate